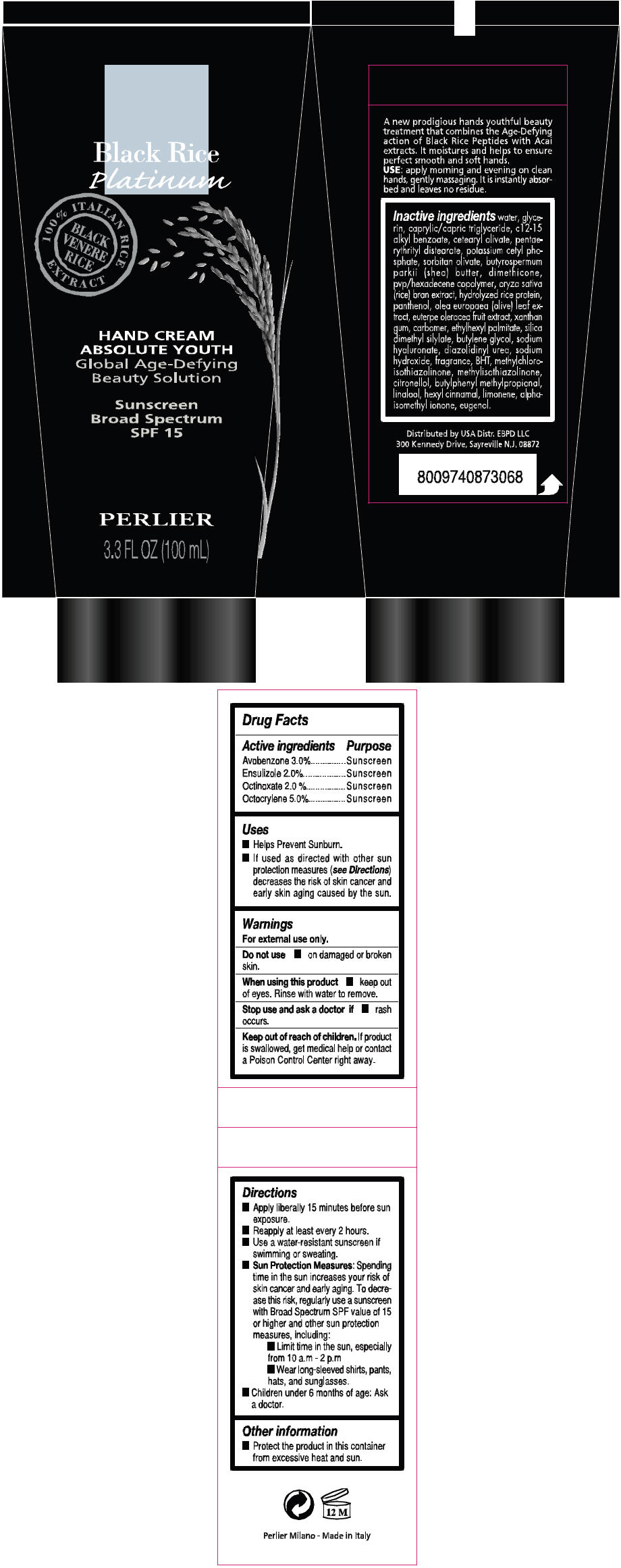 DRUG LABEL: Black Rice Platinum Absolute Youth SPF 15
NDC: 59582-015 | Form: CREAM
Manufacturer: EBPD LLC
Category: otc | Type: HUMAN OTC DRUG LABEL
Date: 20130823

ACTIVE INGREDIENTS: Avobenzone 30 mg/1 mL; Ensulizole 20 mg/1 mL; Octinoxate 20 mg/1 mL; Octocrylene 50 mg/1 mL
INACTIVE INGREDIENTS: Water; Glycerin; Tricaprylin; Alkyl (C12-15) Benzoate; Cetearyl Olivate; Pentaerythritol; Potassium Cetyl Phosphate; Sorbitan Olivate; Sheanut Oil; Dimethicone; Hexadecyl Povidone (4 Hexadecyl Branches/Repeat); Rice Bran; Panthenol; Olea Europaea Leaf; Acai; Xanthan Gum; Carbomer Homopolymer Type B (Allyl Sucrose Crosslinked); Ethylhexyl Palmitate; Silica Dimethyl Silylate; Butylene Glycol; Hyaluronate Sodium

Black Rice Platinum Hand Cream Absolute Youth SPF 15

Drug Facts

ACTIVE INGREDIENT

Active ingredients | Purpose
Avobenzone 3.0% | Sunscreen
Ensulizole 2.0% | Sunscreen
Octinoxate 2.0 % | Sunscreen
Octocrylene 5.0% | Sunscreen

Uses

- Helps Prevent Sunburn.
- If used as directed with other sun protection measures (see Directions) decreases the risk of skin cancer and early skin aging caused by the sun.

Warnings

For external use only.

Do not use on damaged or broken skin.

When using this product keep out of eyes. Rinse with water to remove.

Stop use and ask a doctor if rash occurs.

Keep out of reach of children. If product is swallowed, get medical help or contact a Poison Control Center right away.

Directions

- Apply liberally 15 minutes before sun exposure.
- Reapply at least every 2 hours
- Sun Protection Measures: Spending time in the sun increases your risk of skin cancer and early aging. To decrease this risk, regularly use a sunscreen with Broad Spectrum SPF value of 15 or higher and other sun protection measures, including:
  - Limit time in the sun, especially from 10 a.m – 2 p.m
  - Wear long-sleeved shirts, pants, hats, and sunglasses.
- Children under 6 months of age: Ask a doctor.

Other information

- Protect the product in this container from excessive heat and sun.

Inactive ingredients

WATER, GLYCERIN, CAPRYLIC/CAPRIC TRIGLYCERIDE, C12-15 ALKYL BENZOATE, CETEARYL OLIVATE, PENTAERYTHRITYL DISTEARATE, POTASSIUM CETYL PHOSPHATE, SORBITAN OLIVATE, BUTYROSPERMUM PARKII (SHEA) BUTTER, DIMETHICONE, PVP/HEXADECENE COPOLYMER, ORYZA SATIVA (RICE) BRAN EXTRACT, HYDROLYZED RICE PROTEIN, PANTHENOL, OLEA EUROPAEA (OLIVE) LEAF EXTRACT, EUTERPA OLERACEA FRUIT EXTRACT, XANTHAN GUM, CARBOMER, ETHYLHEXYL PALMITATE, SILICA DIMETHYL SILYLATE, BUTYLENE GLYCOL, SODIUM HYALURONATE, DIAZOLIDINYL UREA, SODIUM HYDROXIDE, FRAGRANCE, BHT, METHYLCHLOROISOTHIAZOLINONE, METHYLISOTHIAZOLINONE, CITRONELLOL, BUTYLPHENYL METHYLPROPIONAL, LINALOOL, HEXYL CINNAMAL, LIMONENE, ALPHA-ISOMETHYL IONONE, EUGENOL.

Distributed in USA Distr.EBPD LLC
300 Kennedy Drive, Sayreville N.J 08872

PRINCIPAL DISPLAY PANEL - 100 mL Tube Label

BLACK RICE PLATINUM
100% ITALIAN RICE EXTRACTS
BLACK VENERE RICE

HAND CREAM ABSOLUTE YOUTH
Global Age-Defying Beauty Solutions

Sun Screen
Broad Spectrum
SPF 15

PERLIER

3.3 FL OZ (100mL)